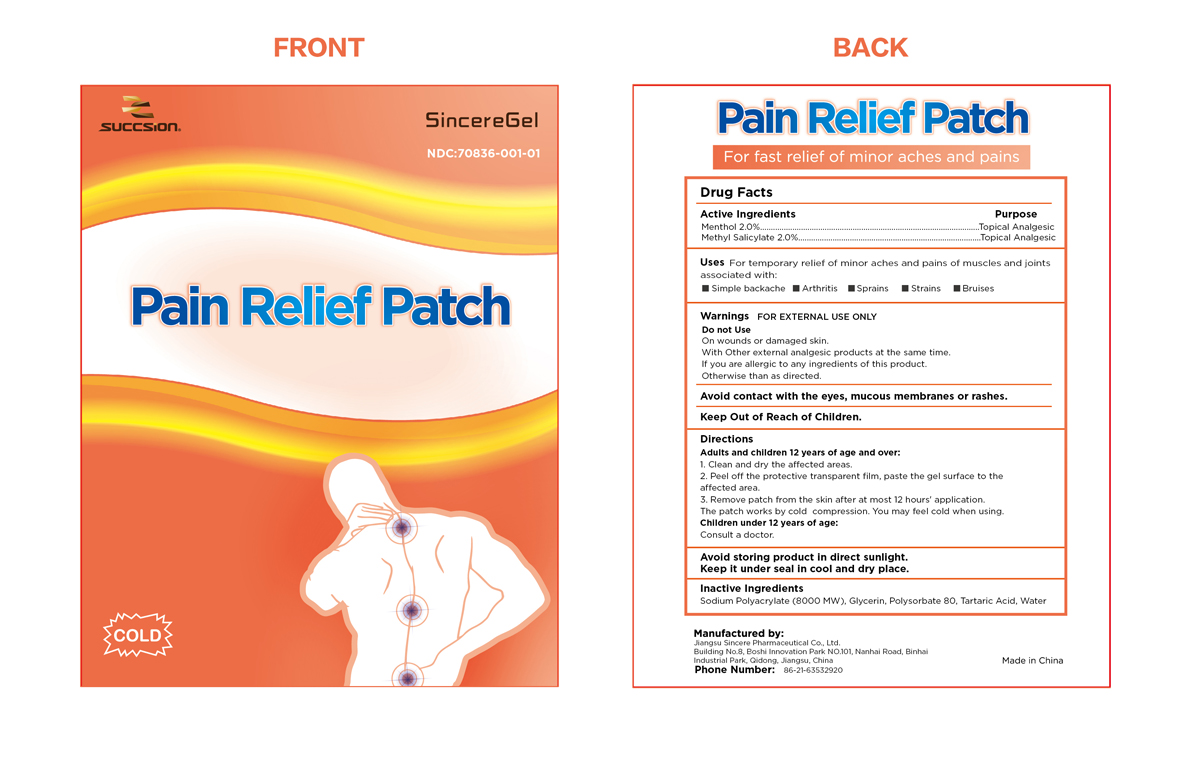 DRUG LABEL: SINCERE PAIN RELIEF
NDC: 70836-001 | Form: PATCH
Manufacturer: Jiangsu Jiangsu Sincere Pharmaceutical Co., Ltd
Category: otc | Type: HUMAN OTC DRUG LABEL
Date: 20161013

ACTIVE INGREDIENTS: MENTHOL 2 g/100 g; METHYL SALICYLATE 2 g/100 g
INACTIVE INGREDIENTS: SODIUM POLYACRYLATE (8000 MW); GLYCERIN; POLYSORBATE 80; TARTARIC ACID; WATER

Jiangsu Sincere Pharmaceutical Co., Ltd

ACTIVE INGREDIENTS

Menthol 2.0%

Methyl Salicylate 2.0%

Purpose

Menthol Topical Analgesic
Methyl Salicylate Topical Analgesic

Uses

For temporary relief of minor aches and pains of muscles and joints associated with:

Simple backache
Arthritis
Sprains
Strains
Bruises

Warnings

For external use only.

Do not Use

On wounds or damaged skin.

With Other external analgesic products at the same time.

If you are allergic to any ingredients of this product.

Otherwise than as directed.

Avoid contact with the eyes, mucous membranes or rashes.

Keep Out of Reach of Children.

Directions

Adults and children 12 years of age and over:
1. Clean and dry the affected areas.
2. Peel off the protective transparent film, paste the gel surface to the affected area.
3. Remove patch from the skin after at most 12 hours' application. The patch works by cold compression. You may feel cold when using.

Children under 12 years of age:
Consult a doctor.

STORAGE AND HANDLING

Avoid storing product in direct sunlight.
Keep it under seal in cool and dry place.

Inactive Ingredients

Sodium Polyacrylate (8000 MW), Glycerin, Polysorbate 80, Tartaric Acid, Water

Manufactured by Jiangsu Sincere Pharmaceutical Co.; Ltd.

Building No.8, Boshi Innovation Park NO.101, Nanhai Road, Binhai Industrial Park, Qidong, Jiangsu, China

Phone Number: 86-21-63532920

Made in China